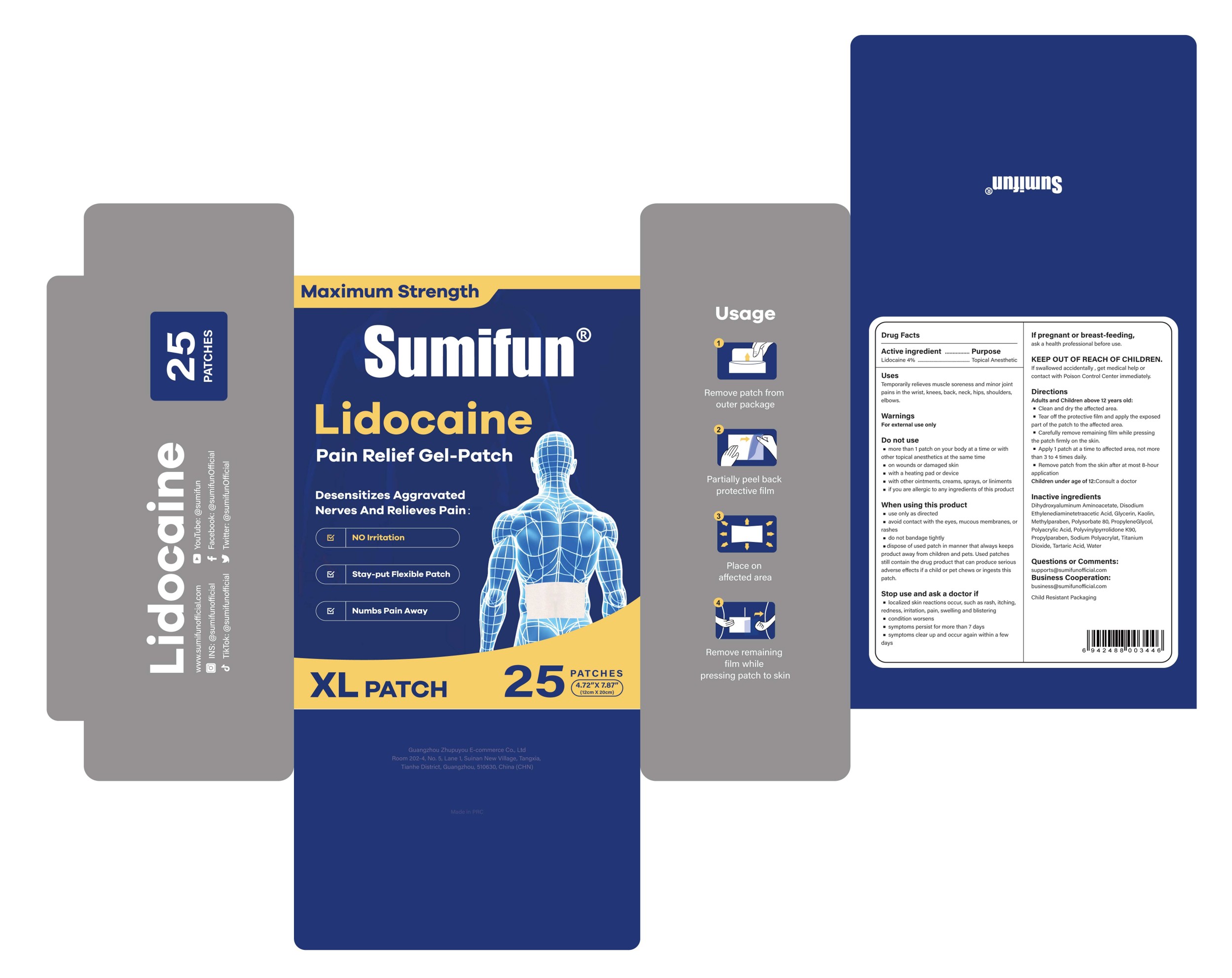 DRUG LABEL: Sumifun Lidocaine Pain Relief Gel-Patch
NDC: 84165-016 | Form: PATCH
Manufacturer: Guangzhou Zhupuyou E-commerce Co., Ltd
Category: otc | Type: HUMAN OTC DRUG LABEL
Date: 20250829

ACTIVE INGREDIENTS: LIDOCAINE 0.04 g/1 g
INACTIVE INGREDIENTS: METHYLPARABEN; POVIDONE K90; TITANIUM DIOXIDE; KAOLIN; PROPYLENE GLYCOL; PROPYLPARABEN; SODIUM POLYACRYLATE (2500000 MW); TARTARIC ACID; WATER; GLYCERIN; POLYSORBATE 80; EDETATE DISODIUM; POLYACRYLIC ACID (250000 MW); DIHYDROXYALUMINUM AMINOACETATE ANHYDROUS

84165-016 Sumifun Lidocaine Pain Relief Gel-Patch

ACTIVE INGREDIENT

Lidocaine 4%

PURPOSE

Topical Anesthetic

INDICATIONS AND USAGE

Temporarily relieves muscle soreness and minor joint pains in the wrist, knees, back, neck, hips, shoulders,elbows.

WARNINGS

For external use only

DO NOT USE

more than 1 patch on your body at a time or with other topical anesthetics at the same time
on wounds or damaged skin
with a heating pad or devicemwith other ointments, creams, sprays, or liniments
if you are allergic to any ingredients of this product

WHEN USING

use only as directed
avoid contact with the eyes, mucous membraneS, orrashes
do not bandage tightly
dispose of used patch in manner that always keeps product away from children and pets. Used patches still contain the drug product that can produce serious adverse effects if a child or pet chews or ingests this patch.

STOP USE

localized skin reactions occur, such as rash, itching,redness, irritation, pain, swelling and blistering
condition worsens
symptoms persist for more than 7 days
symptoms clear up and occur again within a few days

KEEP OUT OF REACH OF CHILDREN

lf swallowed accidentally , get medical help or contact with Poison Control Center immediately.

DOSAGE AND ADMINISTRATION

Adults and Children above 12 years old:
Clean and dry the affected area.
Tear off the protective film and apply the exposed part of the patch to the affected area.
Carefully remove remaining film while pressing the patch firmly on the skin.
Apply 1 patch at a time to affected area, not more than 3 to 4 times daily.
Remove patch from the skin after at most 8-hour application
Children under age of 12:Consult a doctor

INACTIVE INGREDIENT

Dihydroxyaluminum Aminoacetate Anhydrous
Edetate Disodium
Glycerin
Kaolin
Methylparaben
Polyacrylic Acid
Polysorbate 80
PolyvinylPyrrolidone K90
Propylene Glycol
Propylparaben
Sodium Polyacrylate
Tartaric Acid
Titanium Dioxide
Water